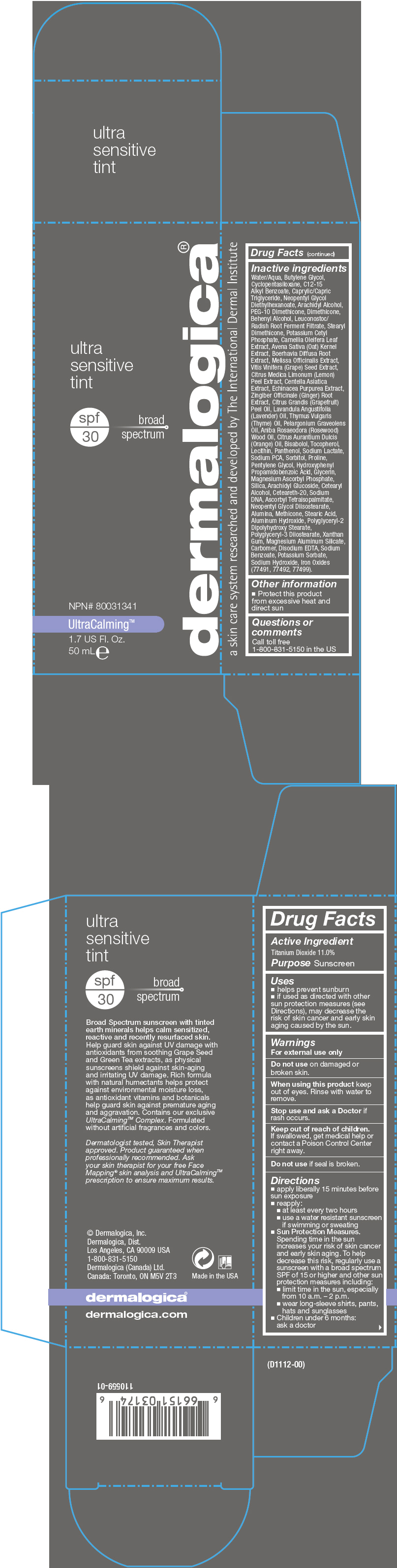 DRUG LABEL: UltraSensitive Tint 
NDC: 68479-120 | Form: LOTION
Manufacturer: Dermalogica, Inc.
Category: otc | Type: HUMAN OTC DRUG LABEL
Date: 20151118

ACTIVE INGREDIENTS: Titanium Dioxide 110 mg/1 mL
INACTIVE INGREDIENTS: Water; Butylene Glycol; Cyclomethicone 5; Alkyl (C12-15) Benzoate; Medium-Chain Triglycerides; Neopentyl Glycol Diethylhexanoate; Arachidyl Alcohol; PEG-10 Dimethicone (600 CST); Dimethicone; Docosanol; Leuconostoc/Radish Root Ferment Filtrate; Stearyl Dimethicone (400 MPA.S at 50C); Potassium Cetyl Phosphate; Camellia Oleifera Leaf; Oat; Boerhavia Diffusa Root; Melissa Officinalis; Vitis Vinifera Seed; Lemon Peel; Centella Asiatica; Echinacea Purpurea; Ginger; Citrus Maxima Fruit Rind Oil; Lavender Oil; Thyme Oil; Geranium Oil, Algerian Type; Rosewood Oil; Orange Oil; Levomenol; Tocopherol; Egg Phospholipids; Panthenol; Sodium Lactate; Sodium Pyrrolidone Carboxylate; Sorbitol; Proline; Pentylene Glycol; Hydroxyphenyl Propamidobenzoic Acid; Glycerin; Magnesium Ascorbyl Phosphate; Silicon Dioxide; Arachidyl Glucoside; Cetostearyl Alcohol; Polyoxyl 20 Cetostearyl Ether; Ascorbyl Tetraisopalmitate; Neopentyl Glycol Diisostearate; Aluminum Oxide; Methicone (20 CST); Stearic Acid; Aluminum Hydroxide; Polyglyceryl-2 Dipolyhydroxystearate; Polyglyceryl-3 Diisostearate; Xanthan Gum; Magnesium Aluminum Silicate; Carbomer Homopolymer Type C (Allyl Pentaerythritol Crosslinked); Edetate Disodium; Sodium Benzoate; Potassium Sorbate; Sodium Hydroxide; Ferric Oxide Red; Ferric Oxide Yellow; Ferrosoferric Oxide

UltraSensitive Tint
SPF 30

Drug Facts

Active Ingredient

Titanium Dioxide 11.0%

Purpose

Sunscreen

Uses

- helps prevent sunburn
- if used as directed with other sun protection measures (see Directions), may decrease the risk of skin cancer and early skin aging caused by the sun.

Warnings

For external use only

Do not use on damaged or broken skin.

When using this product keep out of eyes. Rinse with water to remove.

Stop use and ask a Doctor if rash occurs.

Keep out of reach of children. If swallowed, get medical help or contact a Poison Control Center right away.

Do not use if seal is broken.

Directions

- apply liberally 15 minutes before sun exposure
- reapply:
  - at least every two hours
  - use a water resistant sunscreen if swimming or sweating
- Sun Protection Measures. Spending time in the sun increases your risk of skin cancer and early skin aging. To help decrease this risk, regularly use a sunscreen with a broad spectrum SPF of 15 or higher and other sun protection measures including:
  - limit time in the sun, especially from 10 a.m. – 2 p.m.
  - wear long-sleeve shirts, pants, hats and sunglasses
- Children under 6 months: ask a doctor

Inactive ingredients

Water/Aqua, Butylene Glycol, Cyclopentasiloxane, C12-15 Alkyl Benzoate, Caprylic/Capric Triglyceride, Neopentyl Glycol Diethylhexanoate, Arachidyl Alcohol, PEG-10 Dimethicone, Dimethicone, Behenyl Alcohol, Leuconostoc/Radish Root Ferment Filtrate, Stearyl Dimethicone, Potassium Cetyl Phosphate, Camellia Oleifera Leaf Extract, Avena Sativa (Oat) Kernel Extract, Boerhavia Diffusa Root Extract, Melissa Officinalis Extract, Vitis Vinifera (Grape) Seed Extract, Citrus Medica Limonum (Lemon) Peel Extract, Centella Asiatica Extract, Echinacea Purpurea Extract, Zingiber Officinale (Ginger) Root Extract, Citrus Grandis (Grapefruit) Peel Oil, Lavandula Angustifolia (Lavender) Oil, Thymus Vulgaris (Thyme) Oil, Pelargonium Graveolens Oil, Aniba Rosaeodora (Rosewood) Wood Oil, Citrus Aurantium Dulcis (Orange) Oil, Bisabolol, Tocopherol, Lecithin, Panthenol, Sodium Lactate, Sodium PCA, Sorbitol, Proline, Pentylene Glycol, Hydroxyphenyl Propamidobenzoic Acid, Glycerin, Magnesium Ascorbyl Phosphate, Silica, Arachidyl Glucoside, Cetearyl Alcohol, Ceteareth-20, Sodium DNA, Ascorbyl Tetraisopalmitate, Neopentyl Glycol Diisostearate, Alumina, Methicone, Stearic Acid, Aluminum Hydroxide, Polyglyceryl-2 Dipolyhydroxy Stearate, Polyglyceryl-3 Diiostearate, Xanthan Gum, Magnesium Aluminum Silicate, Carbomer, Disodium EDTA, Sodium Benzoate, Potassium Sorbate, Sodium Hydroxide, Iron Oxides (77491, 77492, 77499).

Other information

- Protect this product from excessive heat and direct sun

Questions or comments

Call toll free
1-800-831-5150 in the US

PRINCIPAL DISPLAY PANEL - 50 mL Tube Carton

dermalogica®

ultra
sensitive
tint

spf
30

broad
spectrum

NPN# 80031341

UltraCalming™

1.7 US Fl. Oz.
50 mL e